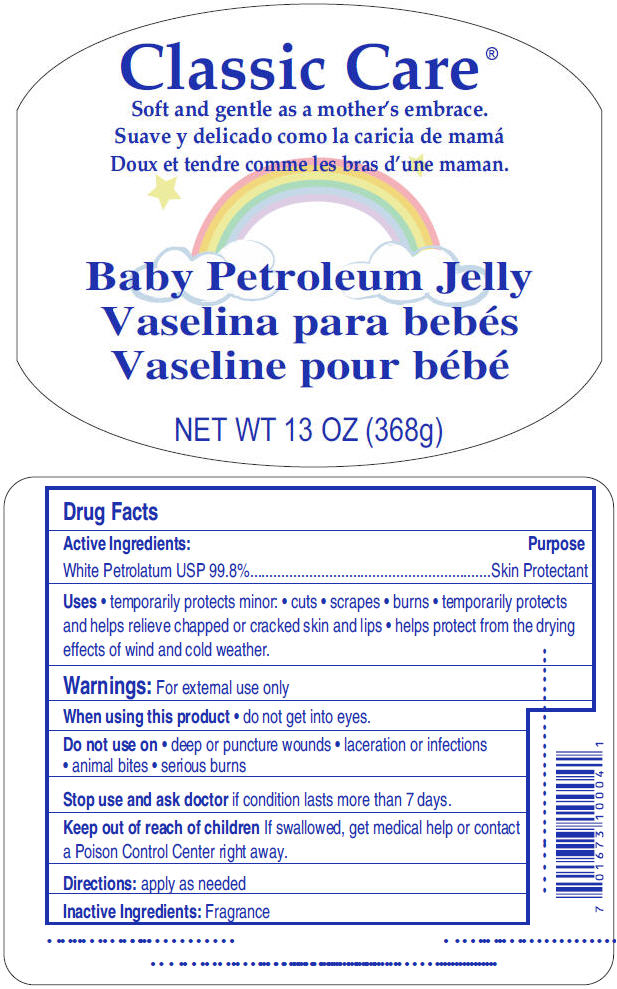 DRUG LABEL: Classic Care 
NDC: 60691-123 | Form: JELLY
Manufacturer: FDN Enterprises, LLC
Category: otc | Type: HUMAN OTC DRUG LABEL
Date: 20131203

ACTIVE INGREDIENTS: Petrolatum 998 mg/1 g

Classic Care ®
Baby

Drug Facts

Active Ingredients

White Petrolatum USP 99.8%

Purpose

Skin Protectant

Uses

- temporarily protects minor:
  - cuts
  - scrapes
  - burns
- temporarily protects and helps relieve chapped or cracked skin and lips
- helps protect from the drying effects of wind and cold weather.

Warnings

For external use only

When using this product

- do not get into eyes.

Do not use on

- deep or puncture wounds
- laceration or infections
- animal bites
- serious burns

Stop use and ask doctor if condition lasts more than 7 days.

Keep out of reach of children If swallowed, get medical help or contact a Poison Control Center right away.

Directions

apply as needed

Inactive Ingredients

Fragrance

PRINCIPAL DISPLAY PANEL - 368 g Bottle Label

Classic Care ®

Soft and gentle as a mother's embrace.

Baby Petroleum Jelly

NET WT 13 OZ (368g)